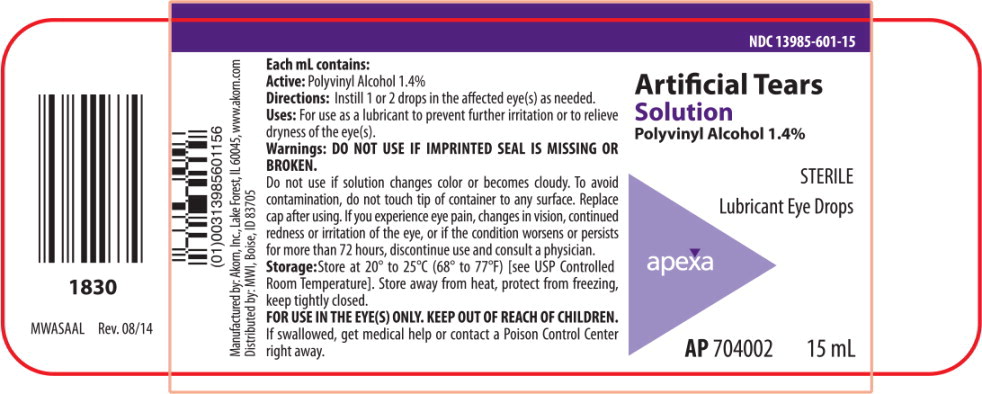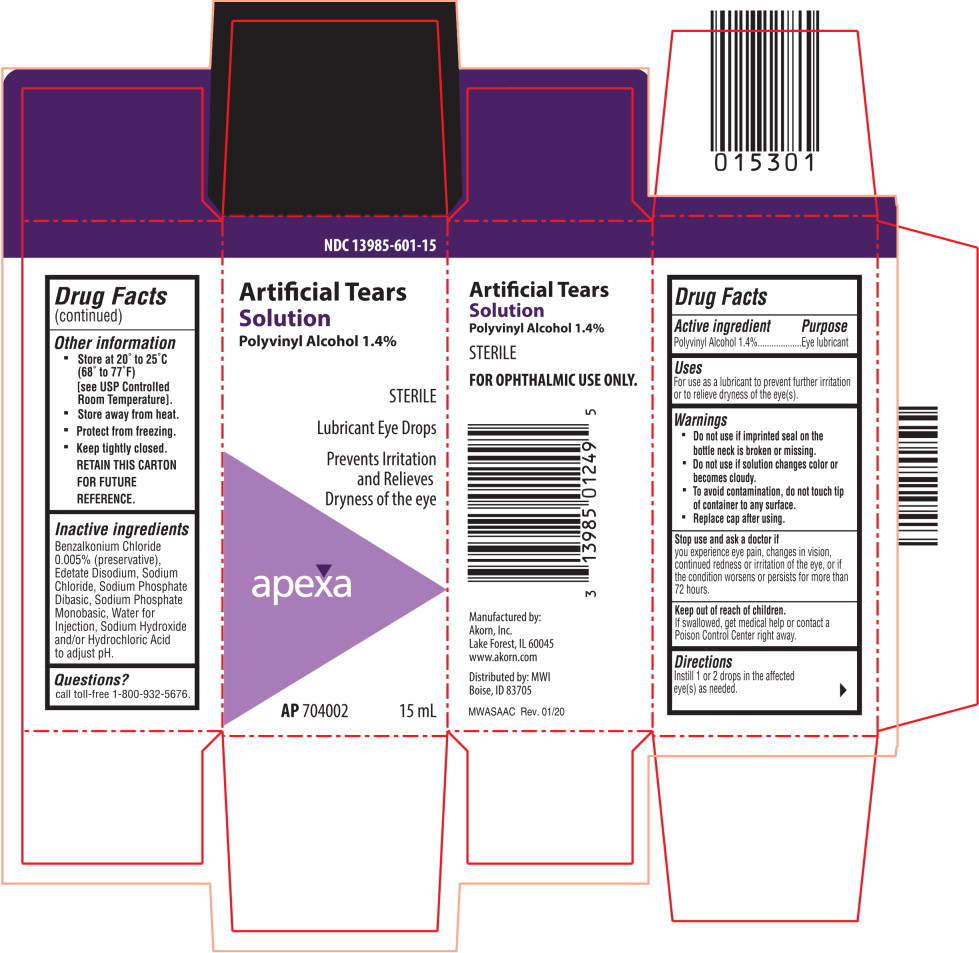 DRUG LABEL: Artificial Tears
NDC: 13985-601 | Form: SOLUTION/ DROPS
Manufacturer: MWI
Category: otc | Type: HUMAN OTC DRUG LABEL
Date: 20220208

ACTIVE INGREDIENTS: POLYVINYL ALCOHOL, UNSPECIFIED 14 mg/1 mL
INACTIVE INGREDIENTS: Benzalkonium Chloride; Edetate Disodium; Sodium Chloride; Sodium Phosphate, Dibasic, Anhydrous; Sodium Phosphate, Monobasic, Anhydrous; Water; Sodium Hydroxide; Hydrochloric Acid

Drug Facts

Active ingredient

Polyvinyl Alcohol 1.4%

Purpose

Eye lubricant

Uses

For use as a lubricant to prevent further irritation or to relieve dryness of the eye(s).

Warnings

- Do not use if imprinted seal on the bottle neck is broken or missing.
- Do not use if solution changes color or becomes cloudy.
- To avoid contamination, do not touch tip of container to any surface.
- Replace cap after using.

Stop use and ask a doctor if you experience eye pain, changes in vision, continued redness or irritation of the eye, or if the condition worsens or persists for more than 72 hours.

Keep out of reach of children. If swallowed, get medical help or contact a Poison Control Center right away.

Directions

Instill 1 or 2 drops in the affected eye(s) as needed.

Other information

- Store at 20° to 25°C (68° to 77°F)
  [see USP Controlled Room Temperature].
- Store away from heat.
- Protect from freezing.
- Keep tightly closed. RETAIN THIS CARTON FOR FUTURE REFERENCE.

Inactive ingredients

Benzalkonium Chloride 0.005% (preservative), Edetate Disodium, Sodium Chloride, Sodium Phosphate Dibasic, Sodium Phosphate Monobasic, Water for Injection, Sodium Hydroxide and/or Hydrochloric Acid to adjust pH.

Questions?

call toll-free 1-800-932-5676.

Principal Display Panel Text for Container Label:

NDC 13985-601-15

Artificial Tears

Solution

Polyvinyl Alcohol 1.4%

STERILE

Lubricant Eye Drops

Apexa logo

AP 704002 15 mL

Principal Display Panel Text for Carton Label:

NDC 13985-601-15

Artificial Tears

Solution

Polyvinyl Alcohol 1.4%

STERILE

Lubricant Eye Drops

Prevents Irritation

and Relieves

Dryness of the eye

Apexa logo

AP 704002 15 mL